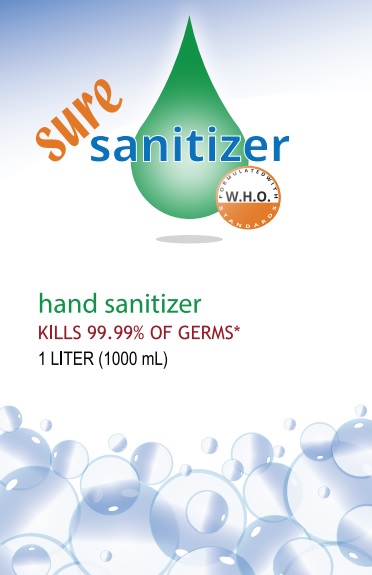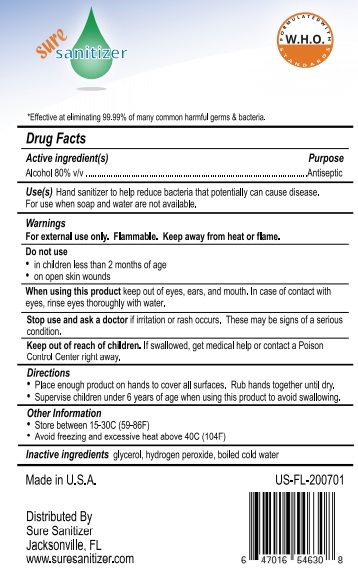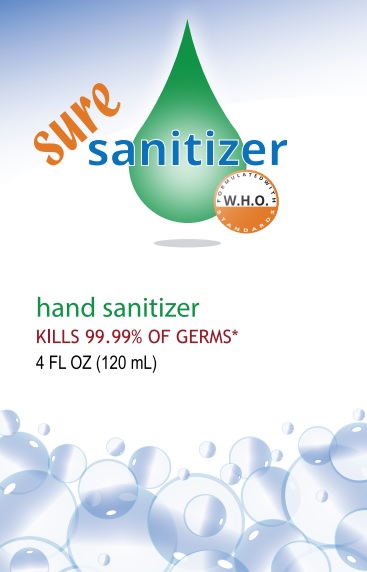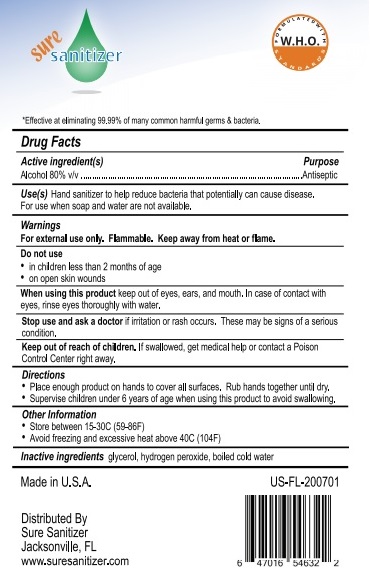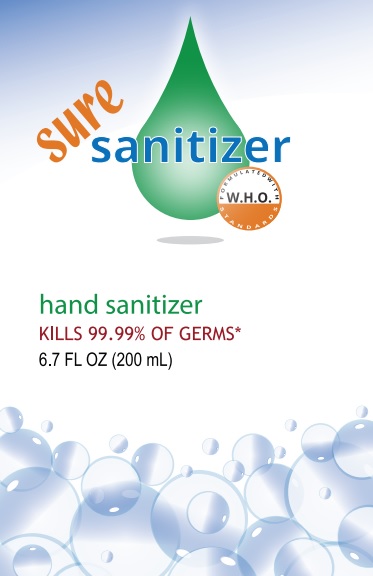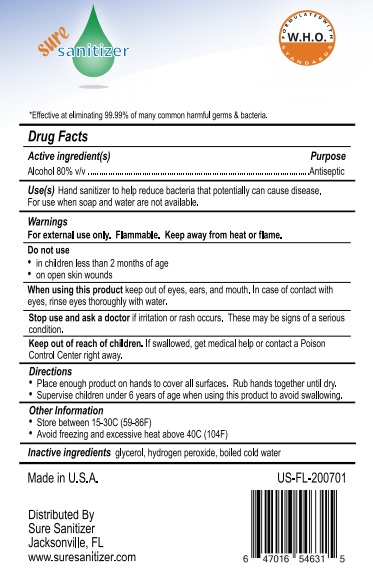 DRUG LABEL: Sure Hand Sanitizer
NDC: 80163-0001 | Form: GEL
Manufacturer: Sir Limited Liability Company
Category: otc | Type: HUMAN OTC DRUG LABEL
Date: 20211110

ACTIVE INGREDIENTS: ALCOHOL 80 mL/100 mL
INACTIVE INGREDIENTS: GLYCERIN 12.5 mL/100 mL; HYDROGEN PEROXIDE 0.125 mL/100 mL; WATER

Sure Sanitizer (Gel):
4 FL OZ (120 mL) NDC: 80163-0001-4
1 LITER (1000 mL) NDC: 80163-0001-1
6.7 FL OZ (200 mL) NDC: 80163-0001-6

Active Ingredient(s)

Alcohol 80% (v/v)

Purpose

Antiseptic

Use

- Hand sanitizer to help reduce bacteria that potentially can cause disease.
- For use when soap and water are not available.

Warnings

For external use only. Flammable. Keep away from heat or flame.

Do not use

- in children less than 2 months of age
- on open skin wounds

WHEN USING

- Keep out of eyes, ears, and mouth. In case of contact with eyes, rinse eyes thoroughly with water.

Stop use and ask a doctor if irritation or rash occurs. These may be signs of a serious condition.

Keep out of reach of children. If swallowed, get medical help or contact a Poison Control Center right away.

Directions

- Place enough product on hands to cover all surfaces. Rub hands together until dry.
- Supervise children under 6 years of age when using this product to avoid swallowing.

Other information

- Store between 15-30C (59-86F)
- Avoid freezing and excessive heat above 40C (104F)

Inactive ingredients

Hydrogen peroxide 0.125% (v/v), glycerol 1.45% (v/v), boiled cold water

Package Label - Principal Display Panel

DISTRIBUTED BY:

Sure Sanitizer

Jacksonville FL

www.suresanitizer.com

Sure Sanitizer (gel):

4 FL OZ (120 mL) NDC: 80163-0001-4

1 LITER (1000 mL) NDC: 80163-0001-1

6.7 FL OZ (200 mL) NDC: 80163-0001-6